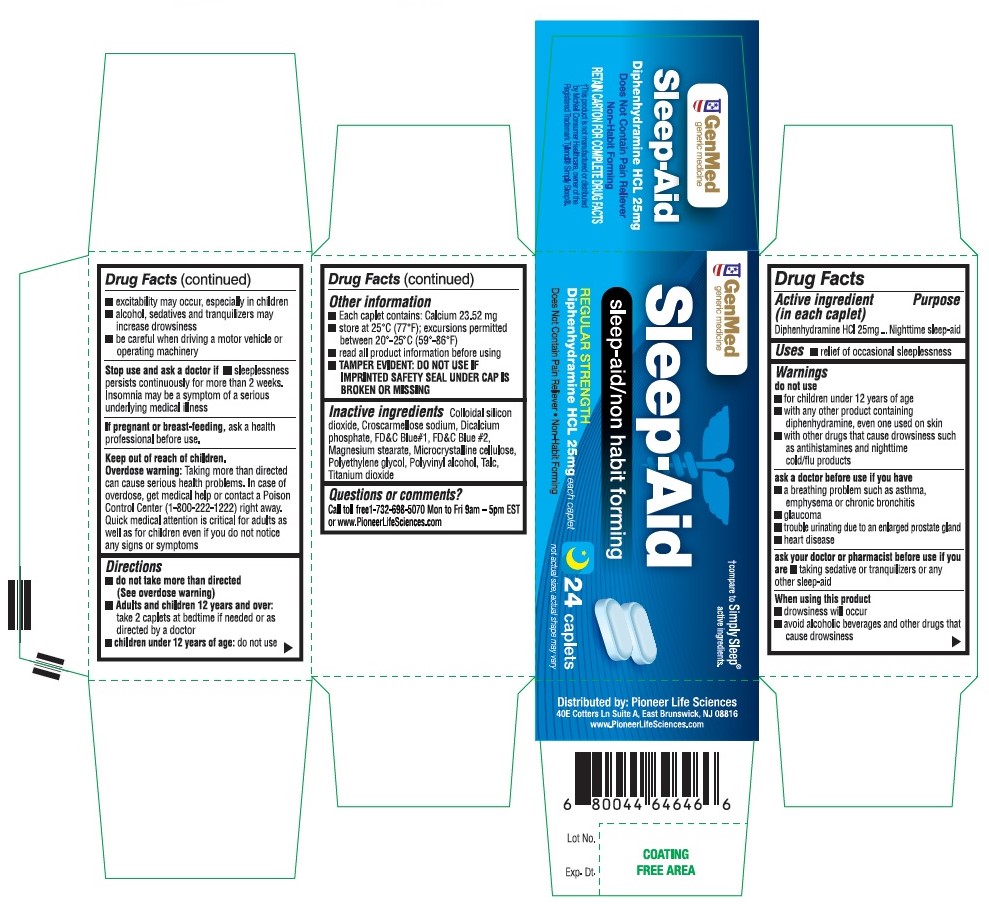 DRUG LABEL: Sleep Aid
NDC: 72090-020 | Form: TABLET
Manufacturer: Pioneer Life Sciences, LLC
Category: otc | Type: HUMAN OTC DRUG LABEL
Date: 20200711

ACTIVE INGREDIENTS: DIPHENHYDRAMINE HYDROCHLORIDE 25 mg/1 1
INACTIVE INGREDIENTS: LECITHIN, SOYBEAN; CELLULOSE, MICROCRYSTALLINE; CROSCARMELLOSE SODIUM; ANHYDROUS DIBASIC CALCIUM PHOSPHATE; SILICON DIOXIDE; MAGNESIUM STEARATE; POLYVINYL ALCOHOL, UNSPECIFIED; TALC; TITANIUM DIOXIDE; POLYETHYLENE GLYCOL, UNSPECIFIED; D&C RED NO. 27 ALUMINUM LAKE

Active Ingredient

Diphenhydramine Hcl 25mg

Purpose

Sleep-aid

Uses:

for relief of occasional sleeplessness

Warnings:

Do not use -

for children under 12 years of age
with any other product containing diphenhydramine, even one used on skin
with other drugs that cause drowsiness

Ask Doctor:

Ask a doctor before use if you have -

a breathing problem such as emphysema or chronic bronchitis
glaucoma
trouble urinating due to an enlarged prostate gland

ASK DOCTOR/PHARMACIST:

Ask a doctor or pharmacist before use if you aretaking sedatives or tranquilizers.

WHEN USING THIS PRODUCT

drowsiness will occur
avoid alcoholic drinks
do not drive a motor vehicle or operating machinery

PREGNANCY

If pregnant or breast-feeding, ask a health professional before use.

KEEP OUT OF REACH OF CHILDREN

Overdose Warning: Taking more than directed can cause serious health problems. In case of overdose, get medical help or contact a Poison Control Center (1-800-222-1222) right away. Quick medical attention is critical for adults as well as for children even if you do not notice any signs or symptoms.

DIRECTIONS

do not take more than directed (see overdose warning)
adults and children 12 years of age and over: - take 2 caplets at bedtime if needed, or as directed by a doctor
children under 12 years of age: do not use

OTHER INFORMATION

each caplet contains: calcium 15 mg
store between 20°-25°C (68°-77°F); avoid high humidity
protect from light
read all product information before using

INACTIVE INGREDIENTS

dicalcium phosphate, microcrystalline cellulose, croscarmellose sodium, colloidal silicon dioxide, magnesium stearate, opadry II

QUESTIONS OR COMMENTS?

Call 1-732-698-5070 Monday through Friday 9AM–5PM EST or www.pioneerlifesciences.com

STOP USE AND ASK A DOCTOR IF

sleeplessness persists continuously for more than 2 weeks. Insomnia may be a symptom of a serious underlying medical illness.